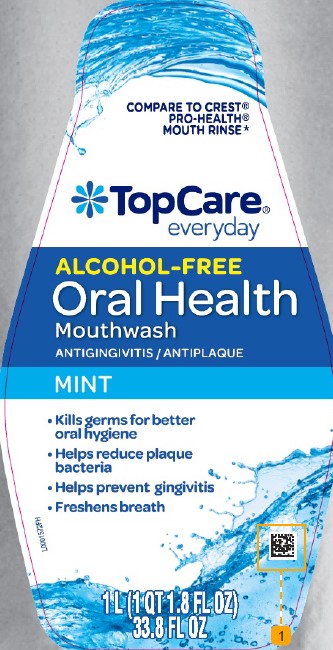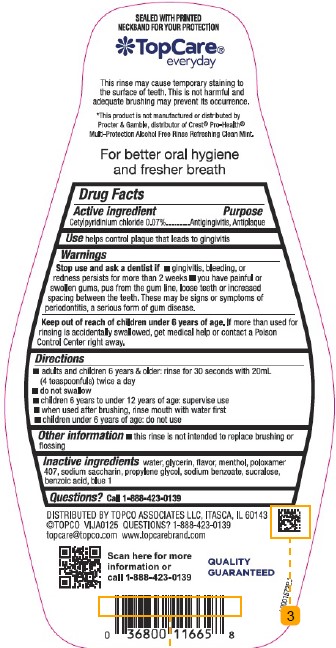 DRUG LABEL: Antiseptic
NDC: 36800-299 | Form: RINSE
Manufacturer: Topco Associates LLC
Category: otc | Type: HUMAN OTC DRUG LABEL
Date: 20260213

ACTIVE INGREDIENTS: CETYLPYRIDINIUM CHLORIDE 0.7 mg/1 mL
INACTIVE INGREDIENTS: WATER; GLYCERIN; MENTHOL, UNSPECIFIED FORM; POLOXAMER 407; SACCHARIN SODIUM; PROPYLENE GLYCOL; SODIUM BENZOATE; SUCRALOSE; BENZOIC ACID; FD&C BLUE NO. 1

TopCare 299.006/299AM
Multi Action Alcohol Free Antiseptic Rinse w/CPC

Tamper Evident Statement

SEALED WITH PRINTED NECKBAND FOR YOUR PROTECTION

Disclaimers/Claims

TopCare

everyday

This rinse may cause temporary staining to the surface of teeth. This is not harmful and adequate brushing may prevent its occurrence.

*This product is not manufactured or distributed by Procter & Gamble, distributor of Crest®Pro-Health®Multi-Protection Alcohol Free Rinse Refreshing Clean Mint.

For better oral hygiene and fresher breath

Active ingredient

Cetylpyridinium chloride 0.07%

Purpose

Antigingivitis, Antiplaque

USE

helps control plaque that leads to gingivitis

Warnings

for this product

Stop use and ask a dentist if

- gingivitis, bleeding or redness persists for more than 2 weeks
- you have painful or swollen gums, pus from the gun line, loose teeth or increased spacing between the teeth. These may be signs or symptoms of periodontitis, a serious form of gum disease.

Keep out of reach of children under 6 years of age.

If more than used for rinsing is accidentally swallowed, get medical help or contact a Poison Control center right away.

Directions

- adults and children 6 years & older: rinse for 30 seconds with 20 mL (4 teaspoonfuls) twice a day
- do not swallow
- children 6 years to under 12 years of age: supervise use
- when used after brushing, rinse mouth with water first
- children under 6 years of age: do not use

other information

- this rinse is not intended to replace brushing or flossing

Inactive ingredients

water, glycerin, flavor, menthol, poloxamer 407, sodium saccharin, propylene glycol, sodium benzoate, sucralose, benzoic acid, blue 1

Questions?

Call 1-888-423-0139

ADVERSE REACTION

DISTRIBUTED BY TOPCO ASSOCIATES, LLC, ITASCA, IL 60143

©TOPCO VIJA0125 QUESTIONS? 1-888-423-0139

topcare@topcare.com www.topcarebrand.com

Scan here for more information or call 1-888-423-0139

QUALITY GUARANTEED

principal display panel

COMPARE TO CREST®PRO-HEALTH®MOUTH RINSE*

TopCare®

everyday

ALCOHOL FREE

ORAL HEALTH

Mouthwash

ANTIGINGIVITIS / ANTIPLAQUE

MINT

- Kills germs for better oral hygiene
- Helps reduce plaque bacteria
- Helps prevent gingivitis
- Freshens breath

1 L (1 QT 1.8 FL OZ) 33.8 FL OZ